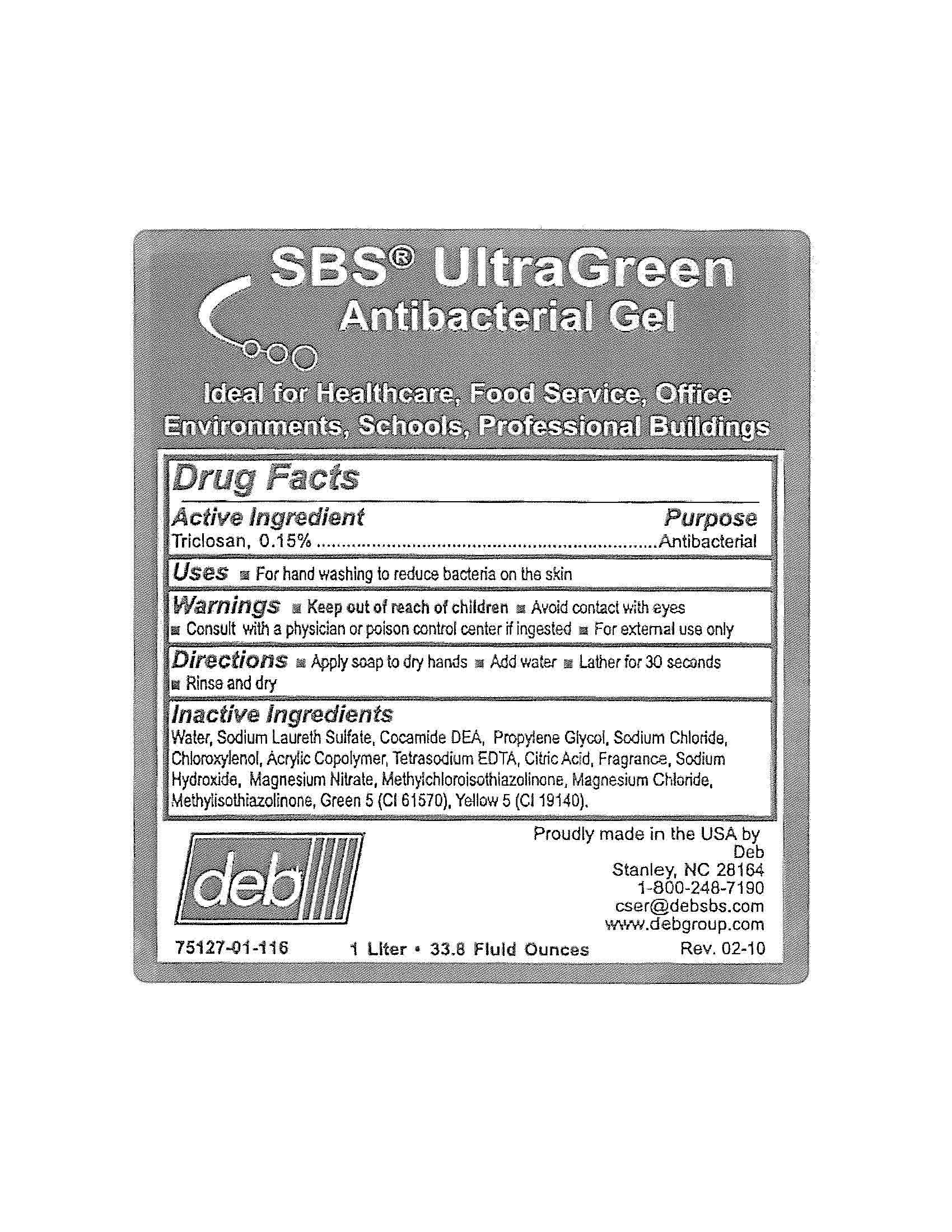 DRUG LABEL: SBS UltraGreen
NDC: 11084-075 | Form: GEL
Manufacturer: Deb USA, Inc.
Category: otc | Type: HUMAN OTC DRUG LABEL
Date: 20100909

ACTIVE INGREDIENTS: TRICLOSAN 0.15 mL/100 mL
INACTIVE INGREDIENTS: WATER; SODIUM LAURETH SULFATE; COCO DIETHANOLAMIDE; PROPYLENE GLYCOL; SODIUM CHLORIDE; CHLOROXYLENOL; EDETATE SODIUM; ANHYDROUS CITRIC ACID; SODIUM HYDROXIDE; D&C GREEN NO. 5; FD&C YELLOW NO. 5; METHYLCHLOROISOTHIAZOLINONE; METHYLISOTHIAZOLINONE; MAGNESIUM NITRATE; MAGNESIUM CHLORIDE

Drug Facts

Active Ingredient

Triclosan, 0.15%

Purpose

Antibacterial

Uses

For handwashing to reduce bacteria on the skin

Warnings

For external use only

Avoid contact with eyes

Keep out of reach of children

Consult with a physician or poison control center if ingested

Directions

Apply soap to dry hands

Add water

Lather for 30 seconds

Rinse and dry

Inactive Ingredients

Water, Sodium Laureth Sulfate, Cocamide DEA, Propylene Glycol, Sodium Chloride, Chloroxylenol, Acrylic Copolymer, Tetrasodium EDTA, Citric Acid, Fragrance, Sodium Hydroxide, Magnesium Nitrate, Methylchloroisothiazolinone, Magnesium Chloride, Methylisothiazolinone, Green 5 (CI 61570), Yellow 5 (CI 19140).

PACKAGE LABEL

SBS UltraGreen

Antibacterial Gel

Ideal for Healthcare, Food Service, Office Environments, Schools, Professional Buildings

Proudly made in the USA

75127-01-116

1 Liter 33.8 Fluid Ounces